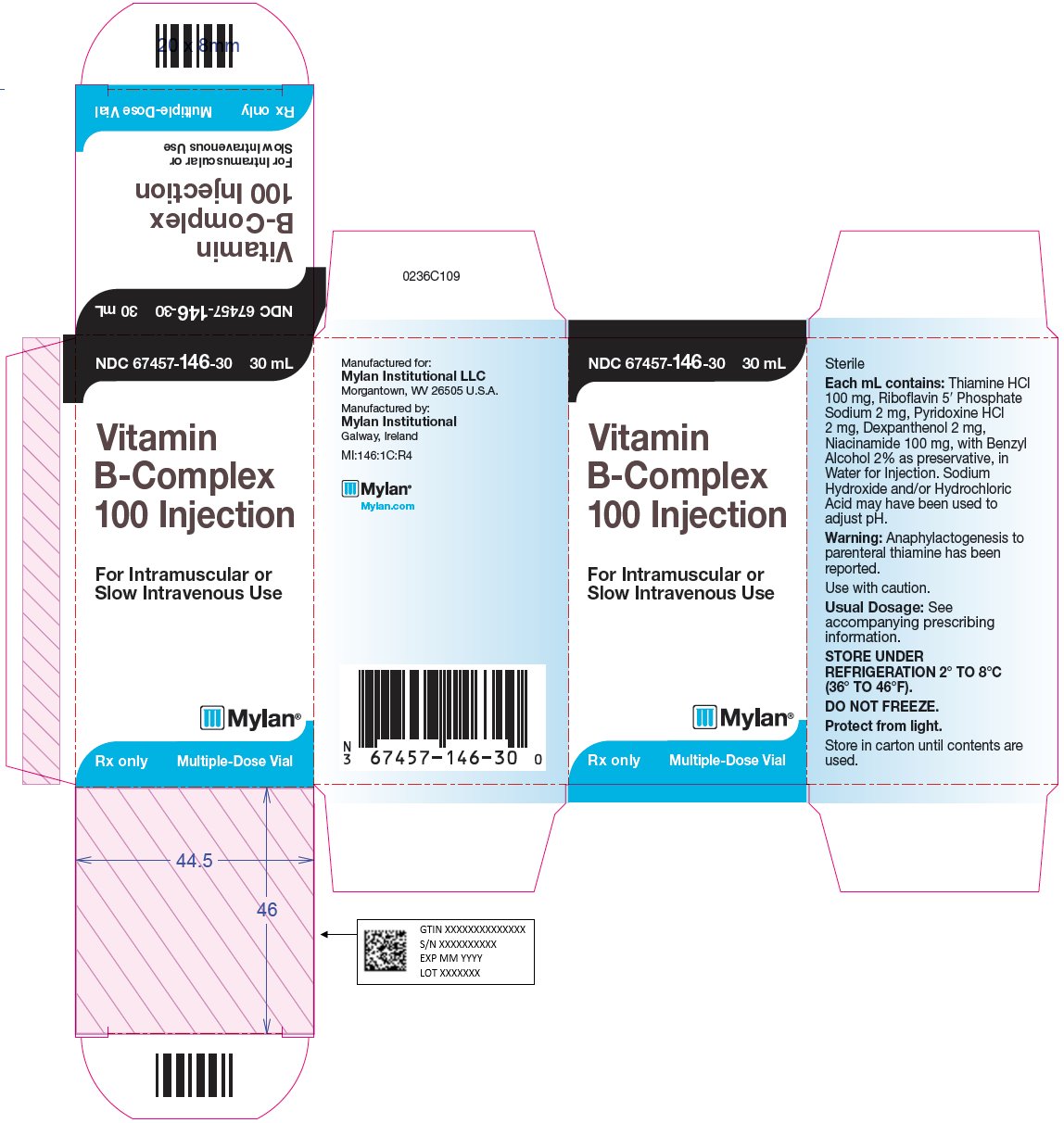 DRUG LABEL: Vitamin B Complex
NDC: 67457-146 | Form: INJECTION
Manufacturer: Mylan Institutional LLC
Category: prescription | Type: HUMAN PRESCRIPTION DRUG LABEL
Date: 20210915

ACTIVE INGREDIENTS: THIAMINE HYDROCHLORIDE 100 mg/1 mL; RIBOFLAVIN 5'-PHOSPHATE SODIUM 2 mg/1 mL; DEXPANTHENOL 2 mg/1 mL; NIACINAMIDE 100 mg/1 mL; PYRIDOXINE HYDROCHLORIDE 2 mg/1 mL
INACTIVE INGREDIENTS: BENZYL ALCOHOL 20 mg/1 mL; WATER; HYDROCHLORIC ACID; SODIUM HYDROXIDE

DESCRIPTION

Vitamin B-Complex 100 Injection is a sterile solution for intramuscular or slow intravenous injection comprised of vitamins which may be categorized as belonging to the vitamin B complex group.

Each mL contains: Thiamine Hydrochloride 100 mg, Riboflavin 5’ Phosphate Sodium 2 mg, Pyridoxine Hydrochloride 2 mg, Dexpanthenol 2 mg, Niacinamide 100 mg, with Benzyl Alcohol 2% as preservative, in Water for Injection. Sodium Hydroxide and/or Hydrochloric Acid may have been used to adjust pH.

INDICATIONS AND USAGE

In disorders requiring parenteral administration of vitamins, i.e. pre- and post-operative treatment, when requirements are increased as in fever, severe burns, increased metabolism, pregnancy, gastrointestinal disorders interfering with intake or absorption of vitamins, prolonged or wasting diseases, alcoholism and where other deficiencies exist.

CONTRAINDICATIONS

Sensitivity to the ingredients listed.

WARNINGS

Anaphylactogenesis may occur with parenteral thiamine. Use with caution. An intradermal test dose is recommended prior to administration in patients suspected of being sensitive to the drug.

PRECAUTIONS

The usual precautions for parenteral administration should be observed. Do not inject if precipitation occurs. Inject slowly by the intravenous route. High concentrations should be diluted using Normal Saline Injection when given intravenously.

ADVERSE REACTIONS

Mild transient diarrhea, polycythemia vera, peripheral vascular thrombosis, itching transitory exanthema, feeling of swelling of entire body, anaphylactic shock and death. Sensitivity to the ingredients listed may occur (see WARNINGS). Use should be discontinued upon observance of any untoward reaction. Pain upon intramuscular injection may be noted.

DOSAGE AND ADMINISTRATION

Usually 0.25 to 2 mL by intramuscular or slow intravenous injection. High concentrations given intravenously may be diluted using parenteral infusion solutions. (See PRECAUTIONS.)

Parenteral drug products should be inspected visually for particulate matter and discoloration prior to administration, whenever the solution and container permit (see HOW SUPPLIED).

HOW SUPPLIED

Vitamin B-Complex 100 Injection is available in a 30 mL multiple-dose vial individually boxed.

Phase separation due to reduced solubility can occur under certain conditions of shipping or storage (e.g. accidental freezing), which may produce visible particles. Do not use product if these do not redissolve on warming to body temperature and shaking well.

Refrigeration of the product may cause darkening of the solution due to the riboflavin content. The colour does not affect the safety or efficacy of the product.

PROTECT FROM LIGHT: Store in carton until contents are used. Store under refrigeration 2° to 8°C (36° to 46°F). Do not permit to freeze.

Manufactured for:
Mylan Institutional LLC
Morgantown, WV 26505 U.S.A.

Manufactured by:
Mylan Institutional
Galway, Ireland

0415L107

Revised: 9/2021
MI:VITBIJ:R4

PRINCIPAL DISPLAY PANEL - 30 mL

NDC 67457-146-30 30 mL

Vitamin
B-Complex
100 Injection

For Intramuscular or
Slow Intravenous Use

Rx only Multi-Dose Vial

Sterile

Each mL contains: Thiamine HCl
100 mg, Riboflavin 5' Phosphate
Sodium 2 mg, Pyridoxine HCl
2 mg, Dexpanthenol 2 mg,
Niacinamide 100 mg, with Benzyl
Alcohol 2% as preservative, in
Water for Injection. Sodium
Hydroxide and/or Hydrochloric
Acid may have been used to
adjust pH.

Warning: Anaphylactogenesis to
parenteral thiamine has been
reported.

Use with caution.

Usual Dosage: See
accompanying prescribing
information.

STORE UNDER
REFRIGERATION 2° TO 8°C
(36° TO 46°F).

DO NOT FREEZE.

Protect from light.

Store in carton until contents are
used.

Manufactured for:
Mylan Institutional LLC
Morgantown, WV 26505 U.S.A.

Manufactured by:
Mylan Institutional
Galway, Ireland

MI:146:1C:R4

Mylan.com